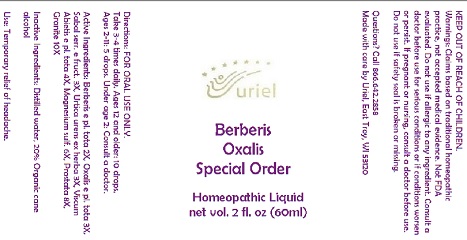 DRUG LABEL: Berberis Oxalis Special Order
NDC: 48951-2139 | Form: LIQUID
Manufacturer: Uriel Pharmacy Inc.
Category: homeopathic | Type: HUMAN OTC DRUG LABEL
Date: 20191125

ACTIVE INGREDIENTS: BERBERIS VULGARIS ROOT BARK 2 [hp_X]/1 mL; OXALIS STRICTA WHOLE 3 [hp_X]/1 mL; SAW PALMETTO 3 [hp_X]/1 mL; URTICA URENS 3 [hp_X]/1 mL; VISCUM ALBUM FRUITING TOP 4 [hp_X]/1 mL; MAGNESIUM SULFATE, UNSPECIFIED FORM 6 [hp_X]/1 mL; BOS TAURUS PROSTATE GLAND 8 [hp_X]/1 mL; PENOXSULAM 10 [hp_X]/1 mL
INACTIVE INGREDIENTS: WATER; ALCOHOL

Berberis Oxalis Special Order

INDICATIONS AND USAGE

Directions: FOR ORAL USE ONLY.

DOSAGE AND ADMINISTRATION

Take 3-4 times daily. Ages 12 and older: 10 drops. Ages 2-11: 5 drops. Under age 2: Consult a doctor.

ACTIVE INGREDIENT

Active Ingredients: Berberis e pl. tota 2X, Oxalis e pl. tota 3X, Sabal serr. e fruct. 3X, Urtica urens ex herba 3X, Viscum Abietis e pl. tota 4X, Magnesium sulf. 6X, Prostata 8X, Granite 10X

Inactive Ingredients: Distilled water, 20% Organic cane alcohol

PURPOSE

Use: Temporary relief of headache.

KEEP OUT OF REACH OF CHILDREN.

WARNINGS

Warnings: Claims based on traditional homeopathic practice, not accepted medical evidence. Not FDA evaluated. Do not use if allergic to any ingredient. Consult a doctor before use for serious conditions or if conditions worsen or persist. If pregnant or nursing, consult a doctor before use. Do not use if safety seal is broken or missing.

Questions? Call 866.642.2858
Made with care by Uriel, East Troy, WI 53120
www.urielpharmacy.com